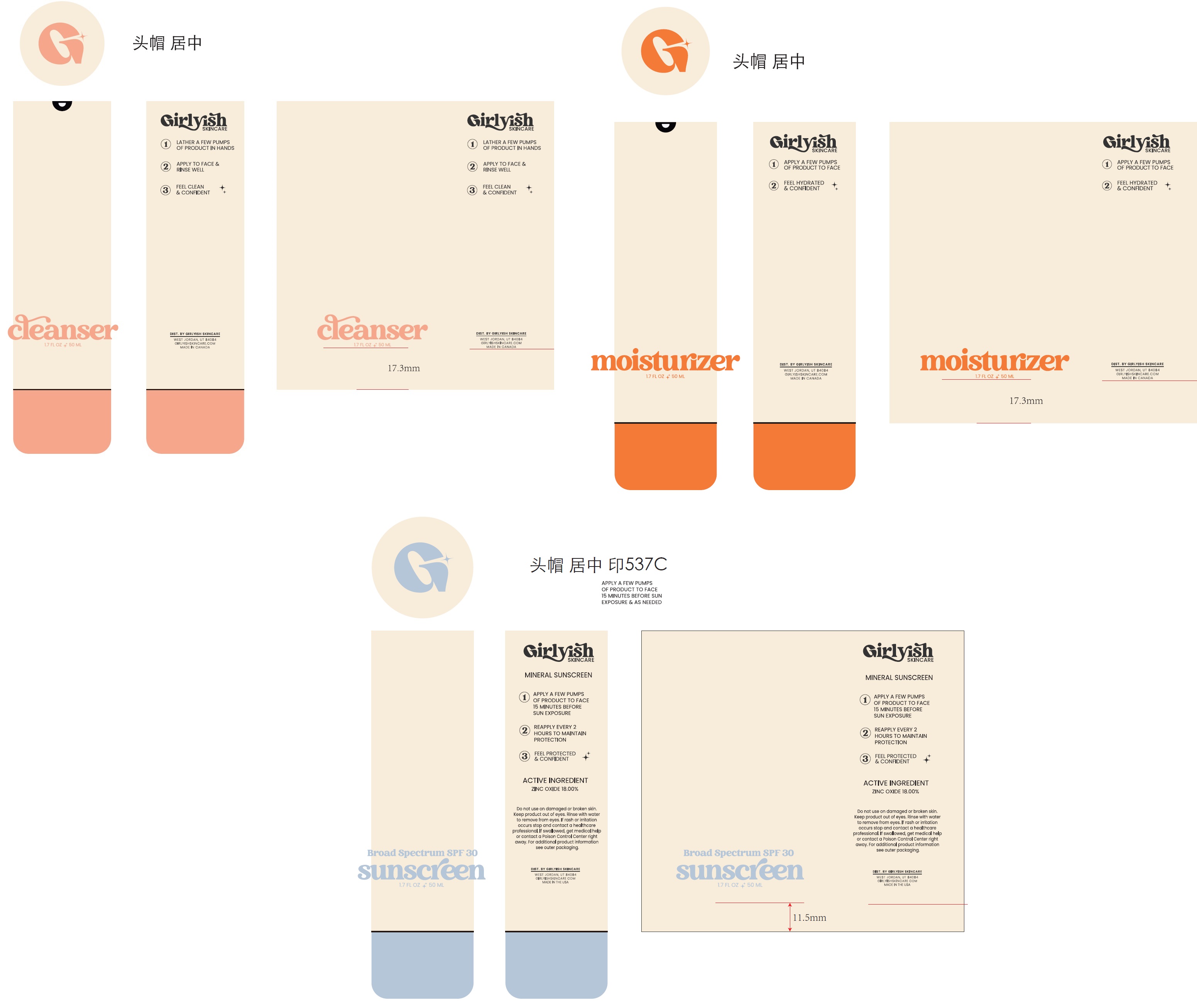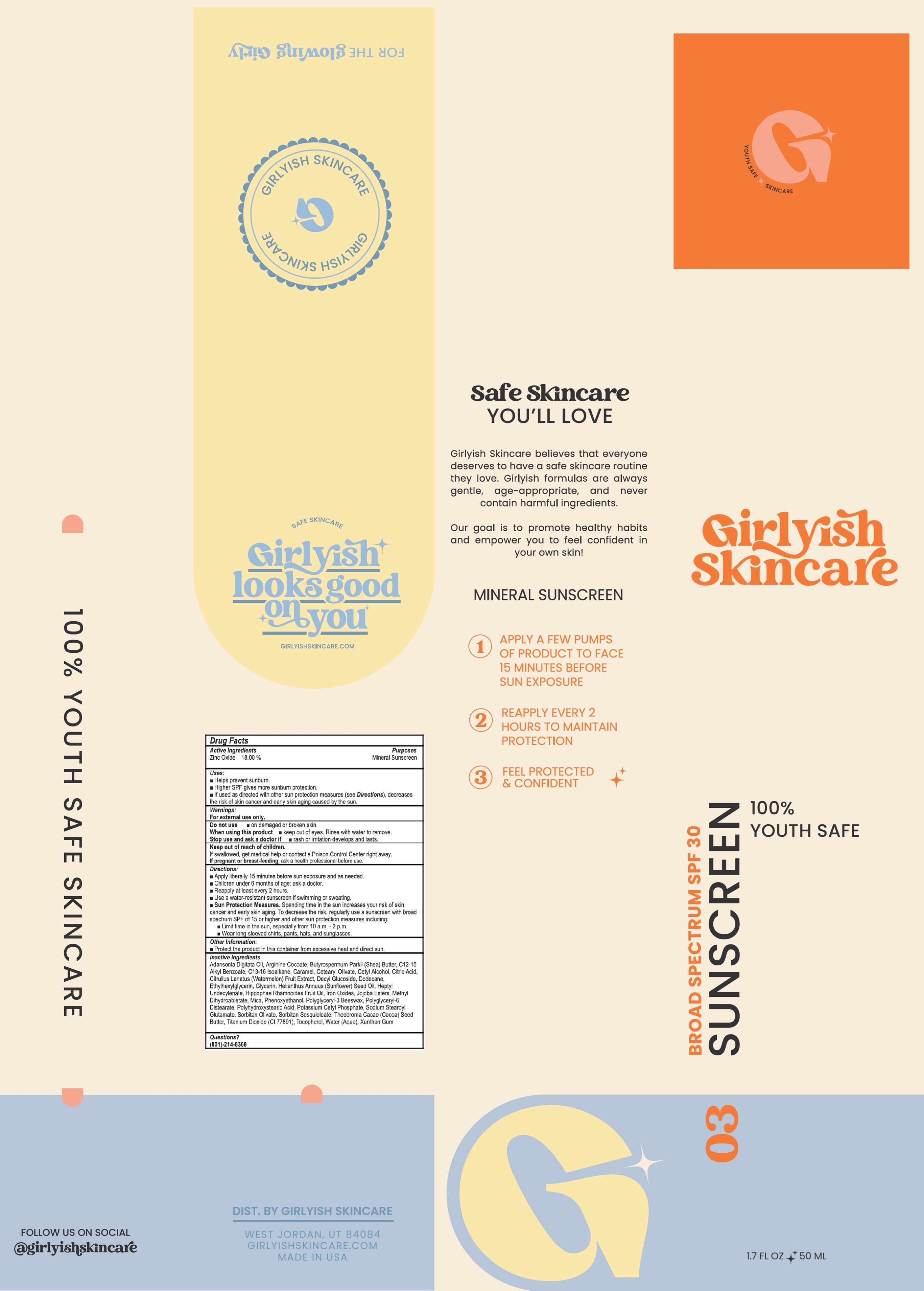 DRUG LABEL: Girlyish Skincare Mineral Sunscreen SPF 30
NDC: 84980-548 | Form: LOTION
Manufacturer: Rise Skincare LLC
Category: otc | Type: HUMAN OTC DRUG LABEL
Date: 20241125

ACTIVE INGREDIENTS: ZINC OXIDE 180 mg/1 mL
INACTIVE INGREDIENTS: ADANSONIA DIGITATA OIL; ARGININE COCOATE; BUTYROSPERMUM PARKII (SHEA) BUTTER; C12-15 ALKYL BENZOATE; C13-16 ISOPARAFFIN; CARAMEL; CETEARYL OLIVATE; CETYL ALCOHOL; CITRIC ACID MONOHYDRATE; WATERMELON; DECYL GLUCOSIDE; DODECANE; ETHYLHEXYLGLYCERIN; GLYCERIN; SUNFLOWER OIL; HEPTYL UNDECYLENATE; HIPPOPHAE RHAMNOIDES FRUIT OIL; IRON OXIDES; METHYL DIHYDROABIETATE; MICA; PHENOXYETHANOL; POLYGLYCERYL-3 BEESWAX; POLYGLYCERYL-6 DISTEARATE; POTASSIUM CETYL PHOSPHATE; SODIUM STEAROYL GLUTAMATE; SORBITAN OLIVATE; SORBITAN SESQUIOLEATE; COCOA BUTTER; TITANIUM DIOXIDE; TOCOPHEROL; WATER; XANTHAN GUM

Girlyish Skincare Mineral Sunscreen SPF 30

Active Ingredients

Zinc Oxide 18.00%

Purpose

Mineral Sunscreen

Uses:

- Helps prevent sunburn.
- Higher SPF gives more sunburn protection.
- If used as directed with other sun protection measures (see Directions), decreases the risk of skin cancer and early skin aging caused by the sun.

Warnings:

For external use only.

Do not use

- on damaged or broken skin.

When using this product

- keep out of eyes. Rinse with water to remove.

Stop use and ask a doctor if

- rash or irritation develops and lasts.

Keep out of reach of children.

If swallowed, get medical help or contact a Poison Control Center right away. If pregnant or breast-feeding, ask a health professional before use.

Directions:

- Apply liberally 15 minutes before sun exposure and as needed.
- Children under 6 months of age: ask a doctor.
- Reapply at least every 2 hours.
- Use a water-resistant sunscreen if swimming or sweating.
- Sun Protection Measures.Spending time in the sun increases your risk of skin cancer and early skin aging. To decrease the risk, regularly use a sunscreen with broad spectrum SPF of 15 or higher and other sun protection meaasures including:
- Limit time in the sun, especially from 10 a.m. - 2 p.m.
- Wear long-sleeved shirts, pants, hats and sunglasses.

Other Information:

- Protect the product in this container from excessive heat and direct sun.

Inactive Ingredients

Adansonia Digitata Oil, Arginine Cocoate, Butyrospermum Parkii (Shea) Butter, C12-15 Alkyl Benzoate, C13-16 Isoalkane, Caramel, Cetearyl Olivate, Cetyl Alcohol, Citric Acid, Cirtullus Lanatus (Watermelon) Fruit Extract, Decyl Glucoside, Dodecane, Ethylhexylglycerin, Glycerin, Hellianthus Annuuss (Sunflower) Seed Oil, Heptyl Undecylenate, Hippophae Rhamnoides Fruit Oil, Iron Oxides, Jojoba Esters, Methyl Dihydroabietate, Mica, Phenoxyethanol, Polyglyceryl-3 Beeswax, Polyglyceryl-6 Distearate, Polyhydroxystearic Acid, Potassium Cetyl Phosphate, Sodium Stearoyl Glutamate, Sorbitan Olivate, Sorbitan Sesquioleate, Theobroma Cacao (Cocoa) Seed Butter, Titanium Dioxide (CI 77891), Tocopherol, Water (Aqua), Xanthan Gum

Questions?

(801)-214-8368